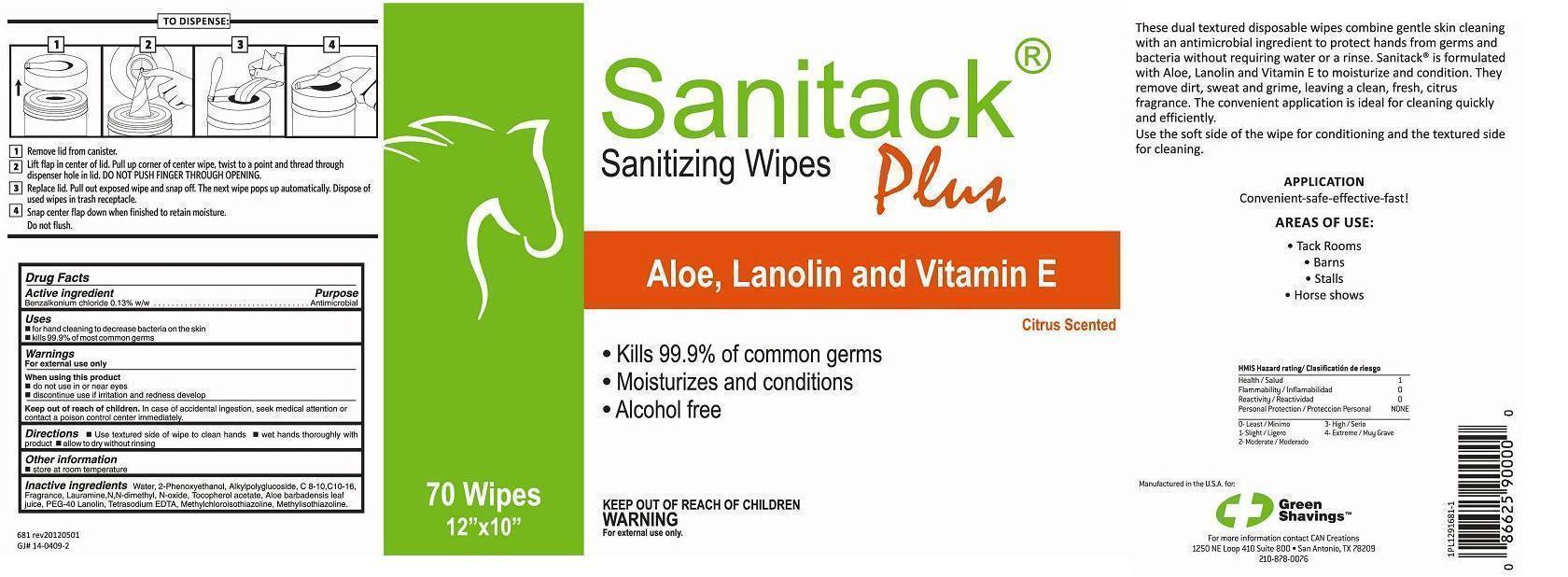 DRUG LABEL: SANITACK SANITIZING WIPES PLUS
NDC: 63401-681 | Form: CLOTH
Manufacturer: CAN Creations
Category: otc | Type: HUMAN OTC DRUG LABEL
Date: 20140414

ACTIVE INGREDIENTS: BENZALKONIUM CHLORIDE 0.01417 g/1 1
INACTIVE INGREDIENTS: WATER; COCAMINE OXIDE; DECYL GLUCOSIDE; METHYLCHLOROISOTHIAZOLINONE; METHYLISOTHIAZOLINONE; ALOE VERA LEAF; LAURAMINE OXIDE; PHENOXYETHANOL; .ALPHA.-TOCOPHEROL ACETATE; EDETATE SODIUM

Active Ingredient

Benzalkonium chloride 0.13% w/w

Purpose

Antimicrobial

Keep out of reach of children

In case of accidental ingestion, seek medical attention or contact a poison control center immediately.

Uses

 for hand cleaning to decrease bacteria on the skin
 kills 99.9% of most common germs

Warnings For external use only

When using this product

 do not use in or near eyes

 discontinue use if irritation and redness develop

Directions

 Use textured side of wipe to clean hands  wet hands thoroughly with product  allow to dry without rinsing

Other information

 store at room temperature

Inactive ingredients:

Water, 2-Phenoxyethanol, Alkylpolyglucoside, C 8-10,C10-16, Lauramine,N,N-dimethyl, N-oxide, Tocopherol acetate, Aloe barbadensis leaf juice, PEG-40 Lanolin, Tetrasodium EDTA, Fragrance, Methylchloroisothiazolinone, Methylisothiazolinone.